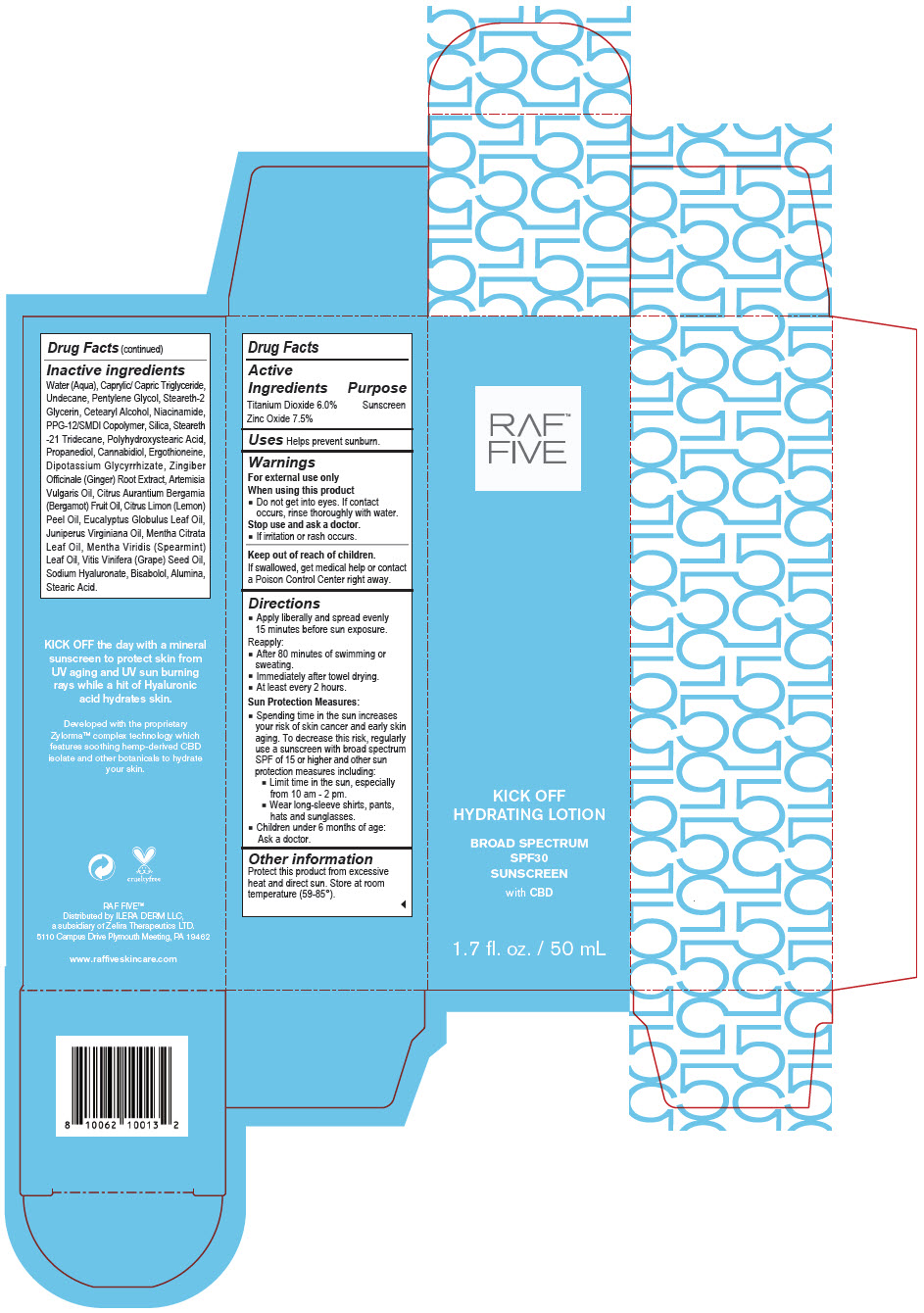 DRUG LABEL: RAF Five - Kick Off Hydrating BROAD SPECTRUM SPF30 SUNSCREEN
NDC: 66163-4453 | Form: LOTION
Manufacturer: Cosmetic Solutions LLC
Category: otc | Type: HUMAN OTC DRUG LABEL
Date: 20210826

ACTIVE INGREDIENTS: Zinc Oxide 7.5 g/100 mL; Titanium Dioxide 6 g/100 mL
INACTIVE INGREDIENTS: Water; Medium-Chain Triglycerides; Undecane; Pentylene Glycol; Steareth-2; Glycerin; Cetostearyl Alcohol; Niacinamide; PPG-12/SMDI Copolymer; Silicon Dioxide; Steareth-21; Tridecane; Propanediol; Cannabidiol; Ergothioneine; Glycyrrhizinate Dipotassium; Ginger; Artemisia Vulgaris Top Oil; Bergamot Oil; Lemon Oil, Cold Pressed; Eucalyptus Oil; Juniperus Virginiana Oil; Spearmint Oil; Grape Seed Oil; Hyaluronate Sodium; Levomenol; Aluminum Oxide; Stearic Acid

RAF™ Five - Kick Off Hydrating Lotion BROAD SPECTRUM SPF30 SUNSCREEN

Drug Facts

Active Ingredients

Titanium Dioxide 6.0%
Zinc Oxide 7.5%

Purpose

Sunscreen

Uses

Helps prevent sunburn.

Warnings

For external use only

When using this product

- Do not get into eyes. If contact occurs, rinse thoroughly with water.

Stop use and ask a doctor.

- If irritation or rash occurs.

Keep out of reach of children.

If swallowed, get medical help or contact a Poison Control Center right away.

Directions

- Apply liberally and spread evenly 15 minutes before sun exposure.

Reapply:

- After 80 minutes of swimming or sweating.
- Immediately after towel drying.
- At least every 2 hours.

Sun Protection Measures:

- Spending time in the sun increases your risk of skin cancer and early skin aging. To decrease this risk, regularly use a sunscreen with broad spectrum SPF of 15 or higher and other sun protection measures including:
  - Limit time in the sun, especially from 10 am - 2 pm.
  - Wear long-sleeve shirts, pants, hats and sunglasses.
- Children under 6 months of age: Ask a doctor.

Other information

Protect this product from excessive heat and direct sun. Store at room temperature (59-85°).

Inactive ingredients

Water (Aqua), Caprylic/ Capric Triglyceride, Undecane, Pentylene Glycol, Steareth-2 Glycerin, Cetearyl Alcohol, Niacinamide, PPG-12/SMDI Copolymer, Silica, Steareth -21 Tridecane, Polyhydroxystearic Acid, Propanediol, Cannabidiol, Ergothioneine, Dipotassium Glycyrrhizate, Zingiber Officinale (Ginger) Root Extract, Artemisia Vulgaris Oil, Citrus Aurantium Bergamia (Bergamot) Fruit Oil, Citrus Limon (Lemon) Peel Oil, Eucalyptus Globulus Leaf Oil, Juniperus Virginiana Oil, Mentha Citrata Leaf Oil, Mentha Viridis (Spearmint) Leaf Oil, Vitis Vinifera (Grape) Seed Oil, Sodium Hyaluronate, Bisabolol, Alumina, Stearic Acid.

Distributed by ILERA DERM LLC,
a subsidiary of Zelira Therapeutics LTD.
5110 Campus Drive Plymouth Meeting, PA 19462

PRINCIPAL DISPLAY PANEL - 50 mL Bottle Carton

RAF™
FIVE

KICK OFF
HYDRATING LOTION

BROAD SPECTRUM
SPF30
SUNSCREEN

with CBD

1.7 fl. oz. / 50 mL